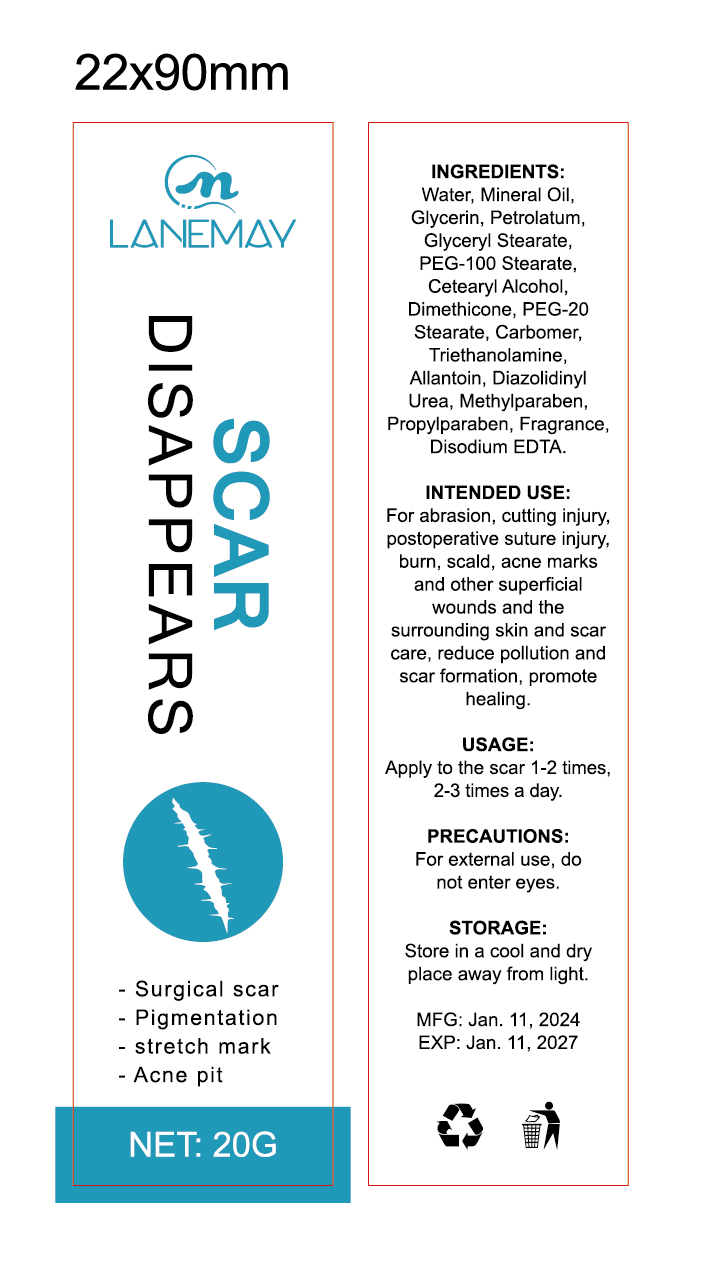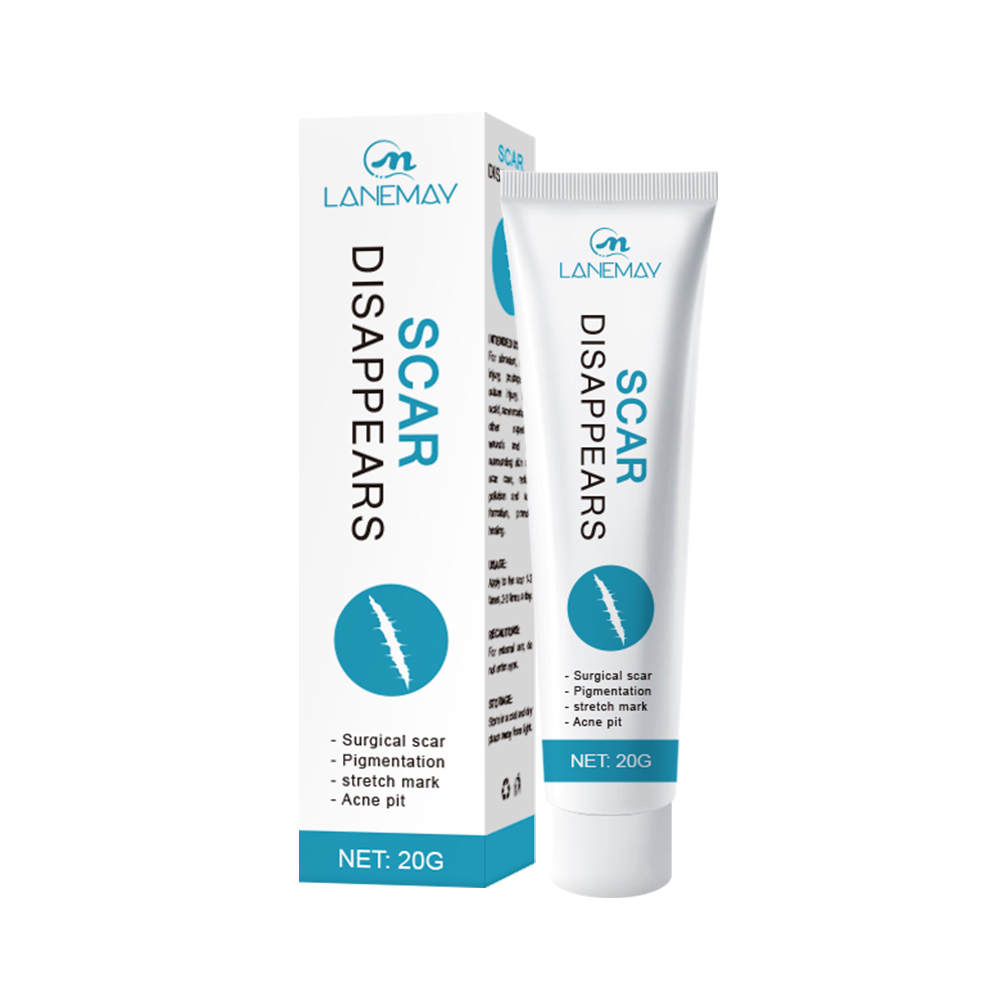 DRUG LABEL: scar beuty cream
NDC: 84025-012 | Form: CREAM
Manufacturer: Guangzhou Yanxi Biotechnology Co., Ltd
Category: otc | Type: HUMAN OTC DRUG LABEL
Date: 20240201

ACTIVE INGREDIENTS: MINERAL OIL 30 mg/20 g
INACTIVE INGREDIENTS: WATER

DOSAGE AND ADMINISTRATION

Put the cream on the scar.

WARNINGS

Please keep it out of children.

INACTIVE INGREDIENT

Water

INDICATIONS AND USAGE

For the normal skin scar recover.